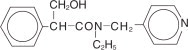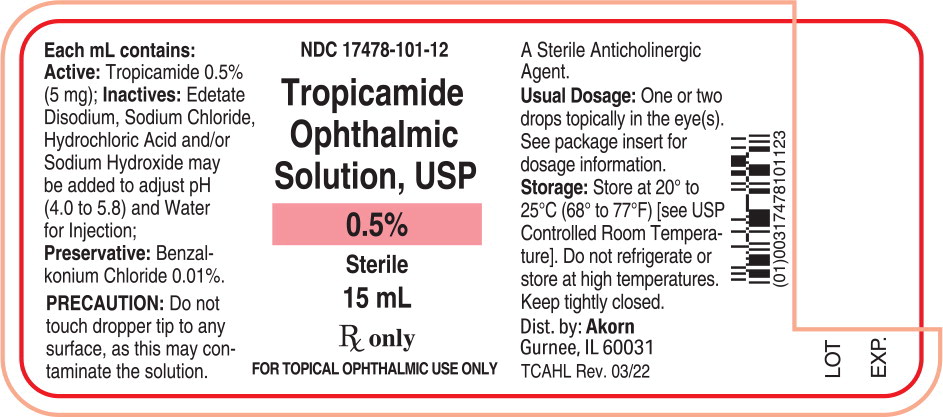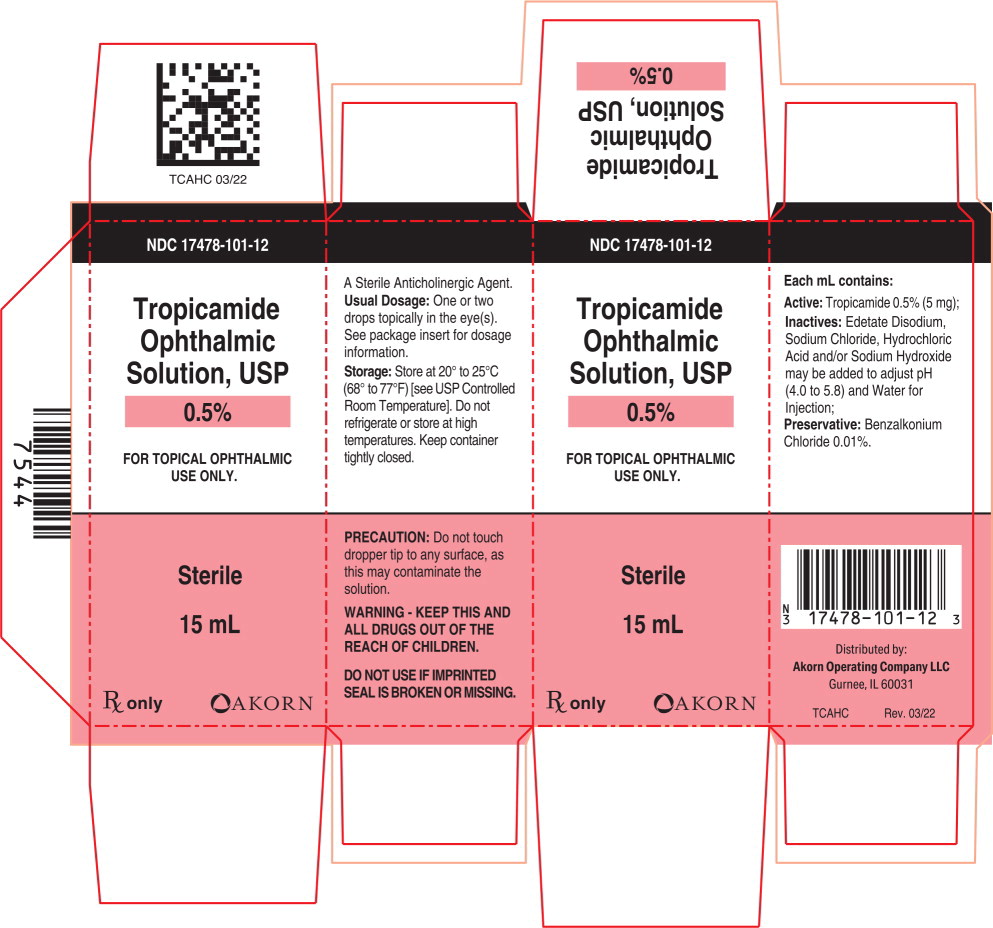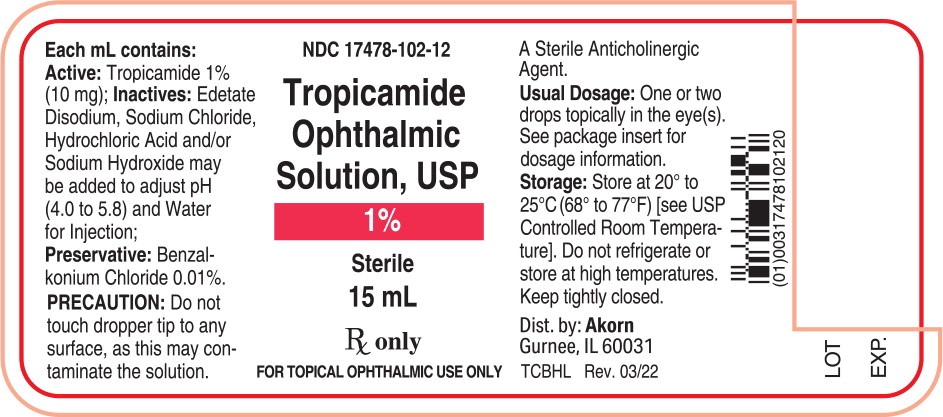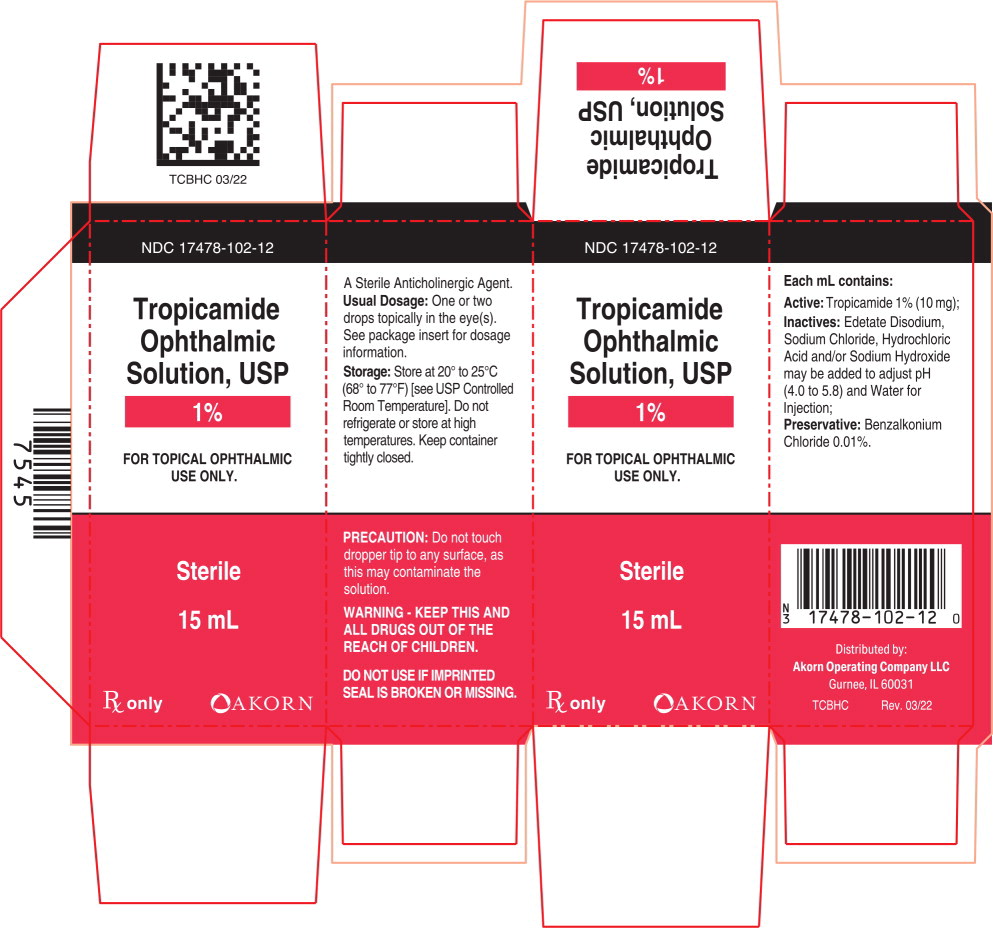 DRUG LABEL: Tropicamide
NDC: 17478-102 | Form: SOLUTION/ DROPS
Manufacturer: Akorn
Category: prescription | Type: HUMAN PRESCRIPTION DRUG LABEL
Date: 20220701

ACTIVE INGREDIENTS: Tropicamide 10 mg/1 mL
INACTIVE INGREDIENTS: benzalkonium chloride; edetate disodium; sodium chloride; sodium hydroxide; hydrochloric acid; water

Tropicamide Ophthalmic Solution, USP

Rx only

DESCRIPTION:

Tropicamide Ophthalmic Solution, USP is an anticholinergic prepared as a sterile topical ophthalmic solution in two strengths. The active ingredient is represented by the structural formula:

C17H20N2O2 MW=284.36

Established name: Tropicamide

Chemical name: Benzeneacetamide, N-ethyl-α-(hydroxymethyl)-N-(4-pyridinylmethyl)-.

Each mL contains: Active: Tropicamide 0.5% (5 mg) or 1% (10 mg). Inactives: Edetate Disodium, Sodium Chloride, Hydrochloric Acid and/or Sodium Hydroxide (to adjust pH), Water for Injection. pH range 4.0 to 5.8. Preservative: Benzalkonium Chloride 0.01%.

CLINICAL PHARMACOLOGY:

This anticholinergic preparation blocks the responses of the sphincter muscle of the iris and the ciliary muscle to cholinergic stimulation, dilating the pupil (mydriasis). The stronger preparation (1%) also paralyzes accommodation. This preparation acts in 15-30 minutes and the duration of activity is approximately 3-8 hours. Complete recovery from mydriasis in some individuals may require 24 hours. The weaker strength may be useful in producing mydriasis with only slight cycloplegia. Heavily pigmented irides may require more doses than lightly pigmented irides.

INDICATIONS AND USAGE:

For mydriasis and cycloplegia for diagnostic procedures.

CONTRAINDICATIONS:

Contraindicated in persons showing hypersensitivity to any component of this preparation.

WARNINGS:

For topical use only — not for injection.

This preparation may cause CNS disturbances which may be dangerous in pediatric patients. The possibility of psychotic reactions and behavioral disturbances due to hypersensitivity to anticholinergic drugs should be considered.

Mydriatics may produce a transient elevation of intraocular pressure.

Remove contact lenses before using.

PRECAUTIONS:

GENERAL PRECAUTIONS

General: The lacrimal sac should be compressed by digital pressure for two to three minutes after instillation to avoid excessive systemic absorption.

PATIENT COUNSELING INFORMATION

Information for Patients: Do not touch dropper tip to any surface, as this may contaminate the solution. Patient should be advised not to drive or engage in potentially hazardous activities while pupils are dilated. Patient may experience sensitivity to light and should protect eyes in bright illumination during dilation. Parents should be warned not to get this preparation in their child's mouth and to wash their own hands and the child's hands following administration.

DRUG INTERACTIONS

Drug Interactions: Tropicamide may interfere with the antihypertensive action of carbachol, pilocarpine, or ophthalmic cholinesterase inhibitors.

CARCINOGENESIS AND MUTAGENESIS AND IMPAIRMENT OF FERTILITY

Carcinogenesis, Mutagenesis, Impairment of Fertility: There have been no long-term studies done using tropicamide in animals to evaluate carcinogenic potential.

PREGNANCY

Pregnancy: Pregnancy Category C. Animal reproduction studies have not been conducted with tropicamide. It is also not known whether tropicamide can cause fetal harm when administered to a pregnant woman or can affect reproduction capacity. Tropicamide should be given to a pregnant woman only if clearly needed.

NURSING MOTHERS

Nursing Mothers: It is not known whether this drug is excreted in human milk. Because many drugs are excreted in human milk, caution should be exercised when tropicamide is administered to a nursing woman.

PEDIATRIC USE

Pediatric Use: Tropicamide may rarely cause CNS disturbances which may be dangerous in pediatric patients. Psychotic reactions, behavioral disturbances, and vasomotor or cardiorespiratory collapse in children have been reported with the use of anticholinergic drugs (See WARNINGS). Keep this and all medications out of the reach of children.

ADVERSE REACTIONS:

Ocular: Transient stinging, blurred vision, photophobia and superficial punctate keratitis have been reported with the use of tropicamide. Increased intraocular pressure has been reported following the use of mydri-atics.

Non-Ocular: Dryness of the mouth, tachycardia, headache, allergic reactions, nausea, vomiting, pallor, central nervous system disturbances and muscle rigidity have been reported with the use of tropicamide. Psychotic reactions, behavioral disturbances, and vasomotor or cardiorespiratory collapse in children have been reported with the use of anticholinergic drugs.

DOSAGE AND ADMINISTRATION:

For refraction, instill one or two drops of 1% solution in the eye(s), repeated in five minutes. If patient is not seen within 20 to 30 minutes, an additional drop may be instilled to prolong mydriatic effect. For examination of fundus, instill one or two drops of 0.5% solution 15 to 20 minutes prior to examination. Individuals with heavily pigmented irides may require higher strength or more doses. Mydriasis will reverse spontaneously with time, typically in 4 to 8 hours. However, in some cases, complete recovery may take up to 24 hours.

HOW SUPPLIED:

Tropicamide Ophthalmic Solution USP, 0.5% and 1% are supplied as sterile solutions in plastic dropper bottles.

0.5% NDC 17478-101-12 (15 mL)
1% NDC 17478-102-12 (15 mL)
1% NDC 17478-102-20 (2 mL)

STORAGE AND HANDLING

STORAGE: Store at 20° to 25°C (68° to 77°F) [see USP Controlled Room Temperature]. Do not refrigerate or store at high temperatures. Keep container tightly closed.

Akorn

Distributed by:
Akorn Operating Company LLC
Gurnee, IL 60031
TC00N Rev. 03/22

Principal Display Panel Text for Container Label:

NDC 17478-101-12

Tropicamide

Ophthalmic

Solution, USP

0.5%

Sterile

15 mL

Rx only

For Topical Ophthalmic Use Only

Principal Display Panel Text for Carton Label:

NDC 17478-101-12

Tropicamide

Ophthalmic

Solution, USP

0.5%

For Topical Ophthalmic

Use only.

Sterile

15 mL

Rx only [Akorn logo]

Principal Display Panel Text for Container Label:

NDC 17478-102-12

Tropicamide

Ophthalmic

Solution, USP

1%

Sterile

15 mL

Rx only

For Topical Ophthalmic Use Only

Principal Display Panel Text for Carton Label:

NDC 17478-102-12

Tropicamide

Ophthalmic

Solution, USP

1%

For Topical Ophthalmic

Use only.

Sterile

15 mL

Rx only [Akorn logo]